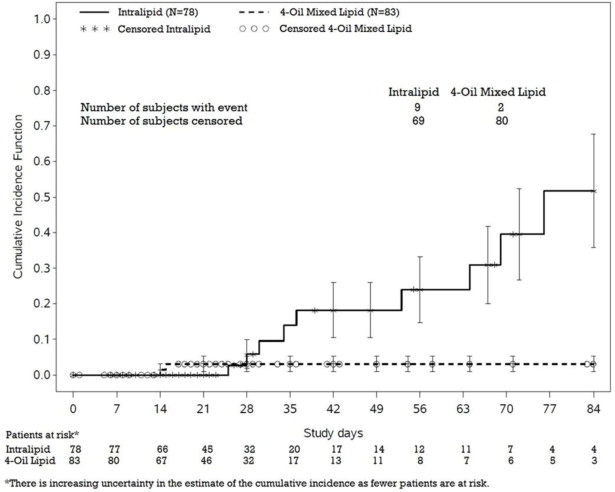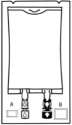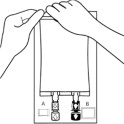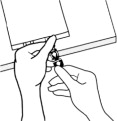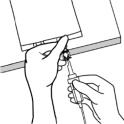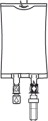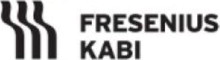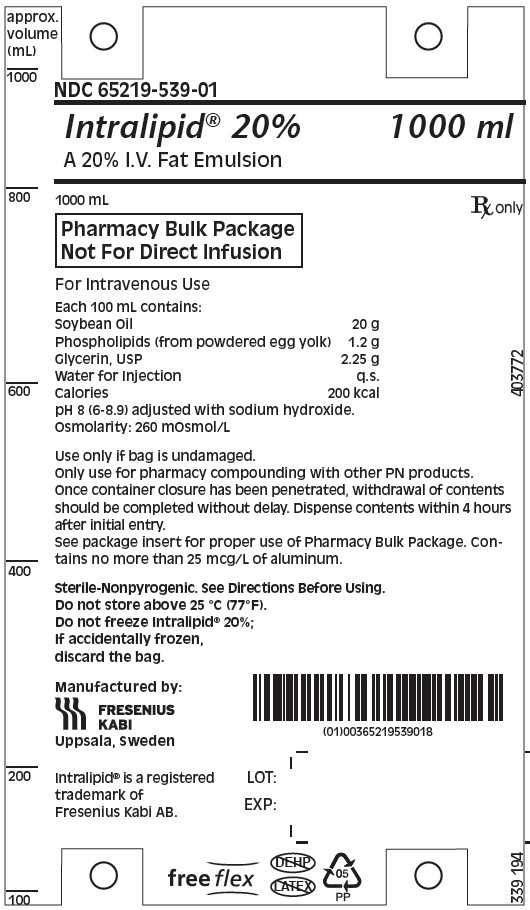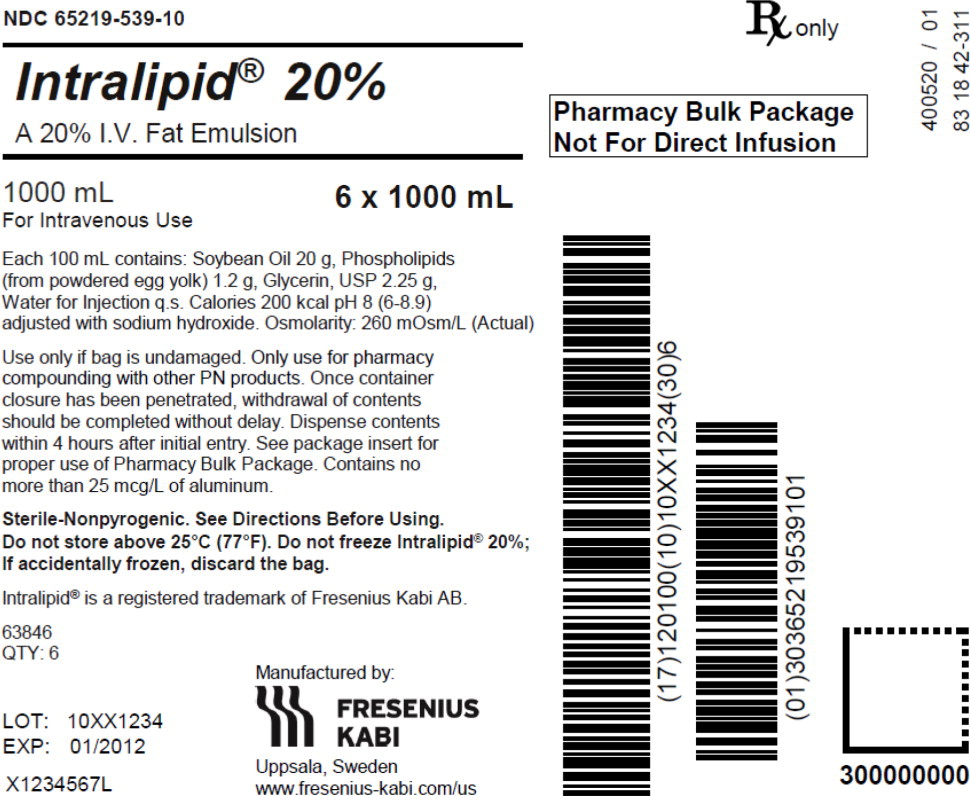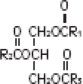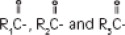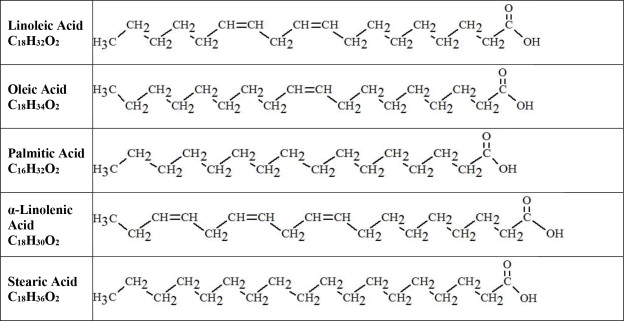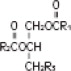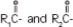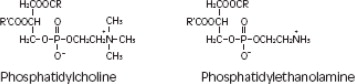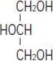 DRUG LABEL: Intralipid
NDC: 65219-539 | Form: EMULSION
Manufacturer: Fresenius Kabi USA, LLC
Category: prescription | Type: HUMAN PRESCRIPTION DRUG LABEL
Date: 20251008

ACTIVE INGREDIENTS: SOYBEAN OIL 20 g/100 mL
INACTIVE INGREDIENTS: EGG PHOSPHOLIPIDS 1.2 g/100 mL; GLYCERIN 2.25 g/100 mL; SODIUM HYDROXIDE; WATER

HIGHLIGHTS OF PRESCRIBING INFORMATION

These highlights do not include all the information needed to use INTRALIPID® safely and effectively. See full prescribing information for INTRALIPID.
INTRALIPID 20% (lipid injectable emulsion), for intravenous use
Initial U.S. Approval: 1975

RECENT MAJOR CHANGES

Warnings and Precautions (5.1) | 7/2025

1 INDICATIONS AND USAGE

Intralipid is indicated as a source of calories and essential fatty acids for adult and pediatric patients requiring parenteral nutrition (PN) and as a source of essential fatty acids for prevention of essential fatty acid deficiency (EFAD).

2 DOSAGE AND ADMINISTRATION

- For intravenous infusion into a peripheral or central vein. (2.1)
- Intralipid Pharmacy Bulk Package is only indicated for use in pharmacy admixture program for the preparation of three-in-one or total nutrition admixtures (TNAs). (2.2)
- Protect the admixed PN solution from light. (2.2, 16)
- Recommended dosage depends on age, energy expenditure, clinical status, body weight, tolerance, ability to metabolize and eliminate lipids, and consideration of additional energy given to the patient. (2.3)

Age | Nutritional Requirements
Age | Initial Recommended Dosage | Maximum Dosage
Birth to 2 years of age (including preterm and term neonates) | 0.5 g/kg/day | 3 g/kg/day
Pediatric patients 2 to <12 years of age | 1 to 2 g/kg/day | 2.5 g/kg/day
Pediatric patients 12 to 17 years of age | 1 g/kg/day | 2 g/kg/day
Adults | 1 g/kg/day (stable) ≤1 g/kg/day (critically ill) | 2.5 g/kg/day

3 DOSAGE FORMS AND STRENGTHS

20% Injectable emulsion:

- 20 g/100 mL (0.2 g/mL) of lipid in 100 mL single-dose flexible container (3)
- 50 g/250 mL (0.2 g/mL) of lipid in 250 mL single-dose flexible container (3)
- 100 g/500 mL (0.2 g/mL) of lipid in 500 mL single-dose flexible container (3)
- 200 g/1,000 mL (0.2 g/mL) of lipid in 1,000 mL Pharmacy Bulk Package (3)

4 CONTRAINDICATIONS

- Known hypersensitivity to egg, soybean, or peanut, or any of the active ingredients or excipients. (4, 5.3)
- Severe disorders of lipid metabolism characterized by hypertriglyceridemia (serum triglyceride > 1,000 mg/dL). (4, 5.7)

5 WARNINGS AND PRECAUTIONS

- Risk of Clinical Decompensation with Rapid Infusion of Intravenous Lipid Emulsion in Neonates and Infants: Acute respiratory distress, metabolic acidosis, and death after rapid infusion of intravenous lipid emulsions have been reported. (5.1, 8.4)
- Risk of Parenteral Nutrition-Associated Liver Disease (PNALD): Increased risk in patients who receive PN for extended periods of time, especially preterm neonates. Monitor liver function tests; if abnormalities occur consider discontinuation or dosage reduction. (5.2, 6.1, 8.4)
- Hypersensitivity Reactions: Monitor for signs or symptoms. Discontinue infusion if reactions occur. (5.3)
- Risk of Infections, Fat Overload Syndrome, Refeeding Syndrome, and Hypertriglyceridemia: Monitor for signs and symptoms; monitor laboratory parameters. (5.4, 5.5, 5.6, 5.7)
- Aluminum Toxicity: Increased risk in patients with renal impairment, including preterm neonates. (5.8, 8.4)

6 ADVERSE REACTIONS

Most common adverse drug reactions (≥5%) from clinical trials in adults were nausea, vomiting, and pyrexia. Most common adverse drug reactions (≥5%) from clinical trials in pediatric patients were anemia, vomiting, increased gamma-glutamyltransferase, and cholestasis. (6.1)

To report SUSPECTED ADVERSE REACTIONS, contact Fresenius Kabi USA, LLC at 1-800-551-7176 or FDA at 1-800-FDA-1088 or www.fda.gov/medwatch.

7 DRUG INTERACTIONS

Vitamin K Antagonists (e.g., warfarin): Anticoagulant activity may be counteracted; increase monitoring of coagulation parameters. (7)

FULL PRESCRIBING INFORMATION

1 INDICATIONS AND USAGE

Intralipid® is indicated as a source of calories and essential fatty acids for adult and pediatric patients requiring parenteral nutrition (PN) and as a source of essential fatty acids for prevention of essential fatty acid deficiency (EFAD).

2 DOSAGE AND ADMINISTRATION

2.1 Important Administration Instructions

- Intralipid is prepared and administered by a healthcare provider in the inpatient setting. Patients and caregivers may prepare and administer Intralipid for home use after appropriate training by a trained healthcare provider.
- Intralipid is for intravenous infusion into a central or peripheral vein.
- Do not exceed the recommended maximum infusion rate in Table 1 [see Dosage and Administration (2.3) and Warnings and Precautions (5.1)].
- Intralipid admixtures with osmolarity
  - Greater than or equal to 900 mOsm/L must be infused through a central vein.
  - Less than 900 mOsm/L may be administered either through a central or peripheral vein.
- Use a 1.2 micron in-line filter during administration.
- Use a dedicated infusion line without any connections. Do not connect multiple medications in series.
- To prevent air embolism, use a non-vented infusion set or close the vent on a vented set and fully evacuate residual gas in the bag prior to administration.
- Do not pressurize the flexible bag to increase flow rates, and if administration is controlled by a pumping device, turn off the pump before the bag runs dry.
- Do not use infusion sets and lines that contain di-2-ethylhexyl phthalate (DEHP), including infusion sets that contain polyvinyl chloride (PVC) components, because they contain DEHP as a plasticizer.
- Intralipid can be infused concurrently into the same vein as dextrose-amino acid solutions (as part of PN) by a Y-connector located near the infusion site; flow rates of each solution should be controlled separately by infusion pumps.
- After connecting the infusion set, start infusion of Intralipid immediately. Complete the infusion within 12 hours when using a Y-connector and within 24 hours when used as part of an admixture.

2.2 Preparation Instructions

Use the following instructions to prepare single-dose 100 mL, 250 mL, and 500 mL Flexible containers for administration:

1. Inspect Bag

- Inspect the integrity indicator (Oxalert®) (A) before removing the overpouch.
- Discard the product if the indicator is black, overpouch is opened or damaged, emulsion color is not white, or seals of bag are broken.

2. Remove Overpouch

- Place the bag on a clean, flat surface.
- Tear the overpouch at notch and pull down.
- Discard the Oxalert sachet (A) and the oxygen absorber (B).
- Visually inspect the bag and contents for particulate matter and discoloration prior to administration. The lipid emulsion should be a homogenous liquid with a milky white appearance. If the mixture is not white or the emulsion has separated (noted by discoloration, phase separation, or oily droplets), or if particulates and/or leakage are observed, discard the bag.

3. Spike Bag

- Identify the infusion port (blue cap with the arrow pointing away from the bag).
- Immediately before inserting the infusion set, break off the blue infusion port cap.
- Use infusion sets according to ISO Number 8536-4 with an external spike diameter of 5.5 to 5.7 mm and use a non-vented infusion set or close the air-inlet on a vented set.
- Use a 1.2 micron in-line filter for administration.
- Hold the base of the infusion port.
- Insert the spike through the infusion port by rotating your wrist slightly until the spike is inserted.
- Do not pierce the infusion port more than once.

4. Hang the bag

- On the hanger cut and start infusion.
- Discard unused portion.

Intralipid 100 mL, 250 mL, and 500 mL single-dose Flexible Containers

- After removing the overpouch, infuse immediately. If not used immediately, the product should be stored at 2°C to 8°C (36°F to 46°F) for no longer than 24 hours. After removal from storage, infuse within 12 hours when using a Y-connector and within 24 hours when used as part of an admixture.

Intralipid 1,000 mL Pharmacy Bulk Package

- For admixing use only and not for direct intravenous infusion. Prior to administration, transfer to a separate PN container for individual patient use.
- Transfer the contents through the blue infusion port using a suitable sterile transfer device or dispensing set. Discard any unused contents.
- Use the Pharmacy Bulk Package immediately for admixing after removal from the overpouch. If not used immediately, the product can be stored for no longer than 24 hours at 2°C to 8°C (36°F to 46°F). After removal from storage, and once the closure is penetrated, use Pharmacy Bulk Package contents within 4 hours.

Admixing Instructions

- Prepare the admixture in PN containers using strict aseptic techniques to avoid microbial contamination.
- Do not add Intralipid to the PN container first; destabilization of the lipid may occur. The prime destabilizers of emulsions are excessive acidity (such as a pH <5) and inappropriate electrolyte content. Amino acid solutions exert buffering effects that protect the emulsion from destabilization. Give careful consideration to the addition of divalent cations (Ca++ and Mg++), which have been shown to cause emulsion instability.
- Do not inject additives directly into Intralipid.
- Intralipid may be mixed with amino acid and dextrose injections to produce “all-in-one” PN admixtures. The mixing sequence below must be followed for manual compounding to minimize pH-related problems by ensuring that typically acidic dextrose injections are not mixed with lipid emulsions alone; shake bags gently after each addition.
  - Transfer dextrose injection to the PN container.
  - Transfer amino acid injection.
  - Transfer Intralipid.
- Simultaneous transfer of amino acid injection, dextrose injection, and Intralipid to the PN container is also permitted; follow automated compounding device instructions as indicated. Use gentle agitation during admixing to minimize localized concentration effects.
- Additions to the PN admixtures should be evaluated by a pharmacist for compatibility. Questions about compatibility may be directed to Baxter Healthcare.
- Inspect the admixture to ensure that precipitates have not formed during preparation of the admixture and the emulsion has not separated. Discard the admixture if any of the above are observed.
- Infuse admixtures containing Intralipid immediately. If not used immediately, store admixtures under refrigeration at 2°C to 8°C (36°F to 46°F) for no longer than 24 hours. Infusion must be complete within 24 hours after removal from refrigeration. Discard any remaining admixture.
- Protect the admixed PN solution from light.

2.3 Recommended Dosage and Administration

- The recommended nutritional requirements of lipid and recommended dosages of Intralipid to be administered to meet those requirements for adults and pediatric patients are provided in Table 1, along with recommendations for the initial and maximum infusion rates.
- The dosing of Intralipid depends on the patient's individual energy requirements influenced by age, body weight, tolerance, clinical status, and the ability to metabolize and eliminate lipids.
- When determining dose, energy supplied by dextrose and amino acids from PN, as well as energy from oral or enteral nutrition, has to be taken into account. Energy and lipid provided from lipid-based medications should also be taken into account (e.g., propofol).
- Prior to administration of Intralipid, correct severe fluid and electrolyte disorders and measure serum triglyceride levels to establish a baseline value. In patients with elevated triglyceride levels, initiate Intralipid at a lower dosage and titrate in smaller increments, monitoring the triglyceride levels with each adjustment [see Warnings and Precautions (5.7)].

Table 1: Recommended Pediatric and Adult Dosage and Infusion Rate
Age | Nutritional Requirements | Direct Infusion Rate
 | Recommended Initial Dosage and Maximum Dosage | Initial | Maximum
Birth to 2 years of age (including preterm and term neonates*) [see Warnings and Precautions (5.1)] | Initial 0.5 g/kg/day not to exceed 3 g/kg/day** | 0.1 mL/kg/hour for the first 10 to 15 minutes; gradually increase to the required rate after 15 minutes | 0.75 mL/kg/hour
Pediatric patients 2 to <12 years of age | Initial 1 to 2 g/kg/day not to exceed 2.5 g/kg/day*** | 0.2 to 0.4 mL/kg/hour for the first 10 to 15 minutes; gradually increase to the required rate after 15 minutes | 0.75 mL/kg/hour
Pediatric patients 12 to 17 years of age | Initial 1 g/kg/day not to exceed 2 g/kg/day** | 0.2 mL/kg/hour for the first 10 to 15 minutes; gradually increase to the required rate after 15 minutes | 0.75 mL/kg/hour
Adults | 1 g/kg/day in stable patients ≤1 g/kg/day in critically ill patients not to exceed 2.5 g/kg/day; not more than 500 mL of Intralipid should be infused on the first day of therapy** | 0.2 mL/kg/hour for the first 10 to 15 minutes; gradually increase to the required rate after 30 minutes | 0.5 mL/kg/hour
* The neonatal period is defined as including term, post-term, and preterm neonates. The neonatal period for term and post-term neonates is the day of birth plus 27 days. For preterm neonates, the neonatal period is defined as the day of birth through the expected age of delivery plus 27 days (i.e., 44 weeks post-menstrual age).
** Daily dosage should also not exceed a maximum of 60% of total energy requirements [see Overdosage (10)].

Dosage Modifications in Patients with Essential Fatty Acid Deficiency

When Intralipid is administered to correct essential fatty acid deficiency (EFAD), supply 8% to 10% of caloric input from Intralipid in order to provide adequate amounts of linoleic and linolenic acids.

3 DOSAGE FORMS AND STRENGTHS

Intralipid 20% is a sterile, homogenous, milky, white lipid injectable emulsion in Flexible Containers supplied as:

- 20 g/100 mL (0.2 g/mL) of lipid in 100 mL single-dose Flexible Container
- 50 g /250 mL (0.2 g/mL) of lipid in 250 mL single-dose Flexible Container
- 100 g/500 mL (0.2 g/mL) of lipid in 500 mL single-dose Flexible Container
- 200 g /1,000 mL (0.2 g/mL) of lipid in 1,000 mL Pharmacy Bulk Package

4 CONTRAINDICATIONS

- Known hypersensitivity to egg, soybean, peanut, or any of the active or inactive ingredients in Intralipid [see Warnings and Precautions (5.3)]
- Severe disorders of lipid metabolism characterized by hypertriglyceridemia (serum triglyceride > 1,000 mg/dL) [see Warnings and Precautions (5.7)]

5 WARNINGS AND PRECAUTIONS

5.1 Clinical Decompensation with Rapid Infusion of Intravenous Lipid Emulsions in Neonates and Infants

In the postmarketing setting, serious adverse reactions including acute respiratory distress, metabolic acidosis, and death have been reported in neonates and infants after rapid infusion of intravenous lipid emulsions. Hypertriglyceridemia was commonly reported.

Strictly adhere to the recommended total daily dosage; the hourly infusion rate should not exceed 0.75 mL/kg/hour [see Dosage and Administration (2.3)].

Preterm and small for gestational age infants have poor clearance of intravenous lipid emulsion and increased free fatty acid plasma levels following lipid emulsion infusion.

Carefully monitor the infant's ability to eliminate the infused lipids from the circulation (e.g., measure serum triglycerides and/or plasma free fatty acid levels). If signs or poor clearance of lipids from the circulation occur, stop the infusion and initiate a medical evaluation [see Warnings and Precautions (5.5, 5.7) and Overdosage (10)].

5.2 Parenteral Nutrition-Associated Liver Disease and Other Hepatobiliary Disorders

Risk of Parenteral Nutrition-Associated Liver Disease

Parenteral nutrition-associated liver disease (PNALD), also referred to as intestinal failure- associated liver disease (IFALD), can present as cholestasis or hepatic steatosis, and may progress to steatohepatitis with fibrosis and cirrhosis (possibly leading to chronic hepatic failure). The etiology of PNALD is multifactorial; however, intravenously administered phytosterols (plant sterols) contained in plant-derived lipid emulsions, including Intralipid, have been associated with development of PNALD.

In a randomized study of neonates and infants expected to be treated with PN for at least 28 days, parenteral nutrition-associated cholestasis (PNAC), a precursor to PNALD, developed more frequently in Intralipid-treated patients than patients treated with a 4-oil mixed lipid emulsion. [see Adverse Reactions (6.1), Use in Specific Populations (8.4)].

Monitor liver tests in patients treated with Intralipid and consider discontinuation or dosage reduction if abnormalities occur.

Other Hepatobiliary Disorders

Hepatobiliary disorders including cholecystitis and cholelithiasis have developed in some PN-treated patients without preexisting liver disease.

Monitor liver tests when administering Intralipid. Patients developing signs of hepatobiliary disorders should be assessed early to determine whether these conditions are related to Intralipid use.

5.3 Hypersensitivity Reactions

Intralipid contains soybean oil and egg phospholipids, which may cause hypersensitivity reactions. Cross reactions have been observed between soybean and peanut. In postmarketing experience, anaphylaxis has been reported following Intralipid administration [see Adverse Reactions (6.2)].

Intralipid is contraindicated in patients with known hypersensitivity to egg, soybean, peanut or any of the active or inactive ingredients in Intralipid [see Contraindications (4)]. If a hypersensitivity reaction occurs, stop infusion of Intralipid immediately and initiate appropriate treatment and supportive measures.

5.4 Infections

Parenteral nutrition, such as Intralipid, can support microbial growth and is an independent risk factor for the development of catheter-related bloodstream infections. To decrease the risk of infectious complications, ensure aseptic techniques are used for catheter placement, catheter maintenance, and preparation and administration of Intralipid.

Monitor for signs and symptoms of infection including fever and chills, as well as laboratory test results that might indicate infection (including leukocytosis and hyperglycemia). Perform frequent checks of the intravenous catheter insertion site for edema, redness, and discharge.

5.5 Fat Overload Syndrome

Fat overload syndrome is a rare condition that has been reported with intravenous lipid injectable emulsions and is characterized by a sudden deterioration in the patient's condition (e.g., fever, anemia, leukopenia, thrombocytopenia, coagulation disorders, hyperlipidemia, hepatomegaly, deteriorating liver function, and central nervous system manifestations such as coma). A reduced or limited ability to metabolize lipids, accompanied by prolonged plasma clearance (resulting in higher lipid levels), may result in this syndrome. Although fat overload syndrome has been most frequently observed when the recommended lipid dose or infusion rate was exceeded, cases have also been described when the lipid formulation was administered according to instructions.

If signs or symptoms of fat overload syndrome occur, stop the infusion of Intralipid. The syndrome is usually reversible when the infusion of the lipid emulsion is stopped.

5.6 Refeeding Syndrome

Administering PN to severely malnourished patients may result in refeeding syndrome, which is characterized by the intracellular shift of potassium, phosphorus, and magnesium as patients become anabolic. Thiamine deficiency and fluid retention may also develop. To prevent these complications, closely monitor severely malnourished patients and slowly increase their nutrient intake.

5.7 Hypertriglyceridemia

The use of Intralipid is contraindicated in patients with hypertriglyceridemia with serum triglyceride concentrations >1,000 mg/dL.

Patients with conditions such as inherited lipid disorders, obesity, diabetes mellitus, or metabolic syndromes have a higher risk of developing hypertriglyceridemia with the use of Intralipid. In addition, patients with hypertriglyceridemia may have worsening of their hypertriglyceridemia with administration of Intralipid. Excessive dextrose administration may further increase such risk.

Evaluate patients' capacity to metabolize and eliminate the infused lipid emulsion by measuring serum triglycerides before the start of infusion (baseline value) and regularly throughout treatment. If triglyceride levels are above 400 mg/dL in adults, stop the Intralipid infusion and monitor serum triglyceride levels to avoid clinical consequences of hypertriglyceridemia such as pancreatitis. In pediatric patients with hypertriglyceridemia, lower triglyceride levels (i.e., below 400 mg/dL) may be associated with adverse reactions. Monitor serum triglyceride levels to avoid potential complications with hypertriglyceridemia such as pancreatitis, lipid pneumonitis, and neurologic changes, including kernicterus.

To minimize the risk of new or worsening of hypertriglyceridemia, assess high-risk patients for their overall energy intake including other sources of lipids and dextrose, as well as concomitant drugs that may affect lipid and dextrose metabolism.

5.8 Aluminum Toxicity

Intralipid contains no more than 25 mcg/L of aluminum. Prolonged PN administration in patients with renal impairment may result in aluminum reaching toxic levels. Preterm neonates are at greater risk because their kidneys are immature, and they require large amounts of calcium and phosphate solutions that contain aluminum.

Patients with impaired kidney function, including preterm neonates, who receive parenteral levels of aluminum at greater than 4 to 5 mcg/kg/day can accumulate aluminum at levels associated with central nervous system and bone toxicity. Tissue loading in these patients may occur at even lower rates of administration.

5.9 Monitoring/Laboratory Tests

Monitor fluid status closely in patients with pulmonary edema or heart failure.

Throughout treatment, monitor serum triglycerides [see Warnings and Precautions (5.7)], essential fatty acids, fluid and electrolyte status, serum osmolarity, blood glucose, liver and kidney function, blood count (including platelets), and coagulation parameters.

The lipids contained in Intralipid may interfere with some laboratory tests (e.g., hemoglobin, lactate dehydrogenase, bilirubin, oxygen saturation) if blood is sampled before lipids have cleared from the bloodstream. Conduct these tests at least 6 hours after stopping the infusion.

Intralipid contains vitamin K that may counteract anticoagulant activity [see Drug Interactions (7)].

6 ADVERSE REACTIONS

Adverse reactions described elsewhere in this Prescribing Information are:

- Clinical Decompensation with Rapid Infusion of Intravenous Lipid Emulsion in Neonates and Infants [see Warnings and Precautions (5.1)]
- Parenteral Nutrition-Associated Liver Disease and Other Hepatobiliary Disorders [see Warnings and Precautions (5.2)]
- Hypersensitivity Reactions [see Warnings and Precautions (5.3)]
- Infections [see Warnings and Precautions (5.4)]
- Fat Overload Syndrome [see Warnings and Precautions (5.5)]
- Refeeding Syndrome [see Warnings and Precautions (5.6)]
- Hypertriglyceridemia [see Warnings and Precautions (5.7)]
- Aluminum Toxicity [see Warnings and Precautions (5.8)]

6.1 Clinical Trials Experience

Because clinical trials are conducted under widely varying conditions, adverse reaction rates observed in the clinical trials of a drug cannot be compared to rates in the clinical trials of another drug and may not reflect the rates observed in clinical practice.

Intralipid or equivalent soybean oil lipid emulsions functioned as the comparator in trials of the 4-oil mixed lipid emulsion [see Clinical Studies (14)]. The adverse reactions from these studies are included to present the clinical experience with Intralipid.

The safety database for Intralipid or equivalent soybean oil lipid emulsion exposure in these studies includes 393 patients (230 adults; 163 pediatric) in 9 clinical trials. Adult patients were exposed for 5 days to 4 weeks in 5 clinical trials. Intralipid or equivalent soybean oil lipid emulsion was used as a component of PN which also included dextrose, amino acids, vitamins, and trace elements. Two of the 5 studies in adults were performed with Intralipid as a component of PN delivered in a 3-chamber bag.

Table 2: Adverse Reactions in >1% of Adult Patients Treated with Intralipid/Soybean oil emulsion
Adverse Reaction | Number of Patients in Soybean Oil Lipid Emulsion Group (N=230) | Number of Patients in 4-Oil Mixed Lipid Emulsion Comparator Group (N=229)
Nausea | 26 (11%) | 20 (9%)
Vomiting | 12 (5%) | 15 (7%)
Pyrexia | 11 (5%) | 9 (4%)
Hypertension | 9 (4%) | 6 (3%)
Headache | 7 (3%) | 3 (1%)
Hyperglycemia | 5 (2%) | 12 (5%)
Abdominal pain | 5 (2%) | 8 (4%)
Flatulence | 4 (2%) | 10 (4%)
Blood triglycerides increased | 4 (2%) | 6 (3%)
Sepsis | 4 (2%) | 5 (2%)
Diarrhea | 4 (2%) | 3 (1%)
Pneumonia | 4 (2%) | 3 (1%)
Pruritus | 4 (2%) | 3 (1%)
Gamma-glutamyltransferase increased | 4 (2%) | 2 (1%)

Less common adverse reactions occurring in ≤1% of adult patients who received Intralipid or equivalent soybean oil lipid emulsion were dyspepsia, urinary tract infection, anemia, infection, dyspnea, cholestasis, dysgeusia, increased blood alkaline phosphatase, tachycardia, liver function test abnormalities, dizziness, rash, and thrombophlebitis.

The 163 patients treated with Intralipid in four pediatric trials consisted of 147 patients <28 days of age, 9 patients 28 days to <2 years of age, and 7 patients 2 to 7 years of age; the duration of exposure was 7 to 84 days. Fifty-six percent of the pediatric patients were female, and 85% were Caucasian. Most pediatric patients were preterm neonates with feeding intolerance or other conditions requiring short-term (<29 days) PN.

Table 3: Adverse Reactions in >1% of Pediatric Patients Treated with Intralipid
Adverse Reaction | Number of Patients in Intralipid Group (N=163) | Number of Patients in 4-Oil Mixed Lipid Emulsion Comparator Group (N=170)
Anemia | 33 (20%) | 30 (18%)
Vomiting | 16 (10%) | 16 (9%)
Gamma-glutamyltransferase increased | 12 (7%) | 10 (6%)
Cholestasis | 10 (6%) | 7 (4%)
Pyrexia | 7 (4%) | 7 (4%)
C-reactive protein increased | 7 (4%) | 6 (4%)
Hyperbilirubinemia | 7 (4%) | 5 (3%)
Bilirubin conjugated increased | 7 (4%) | 3 (2%)
Nosocomial infection | 6 (4%) | 10 (6%)
Blood alkaline phosphatase increased | 6 (4%) | 1 (1%)
Abdominal pain | 5 (3%) | 4 (2%)
Hematocrit decreased | 5 (3%) | 2 (1%)
Metabolic acidosis | 5 (3%) | 2 (1%)
Diarrhea | 4 (3%) | 3 (2%)
Tachycardia | 4 (3%) | 3 (2%)
Thrombocytopenia | 4 (3%) | 3 (2%)
Alanine aminotransferase increased | 3 (2%) | 1 (1%)
Aspartate aminotransferase increased | 3 (2%) | 0 (0%)
Parenteral nutrition-associated liver disease | 3 (2%) | 0 (0%)

Less common adverse reactions occurring in ≤1% of pediatric patients who received Intralipid were hyperglycemia, sepsis, increased blood triglycerides, infection, fluid overload, hypertension, hypertriglyceridemia, rash, and hyperlipidemia.

In a randomized active-controlled, double-blind, parallel-group, multi-center study that included 152 neonates and 9 patients ranging in age from 29 to 153 days who were expected to require PN for at least 28 days, PNAC, a precursor to PNALD, developed more frequently in Intralipid-treated patients than in patients treated with a comparator 4-oil mixed lipid emulsion.

PNAC (defined as direct bilirubin >2 mg/dL with a second confirmed elevation >2 mg/dL at least 7 days later) occurred in 11.5% (9/78) in Intralipid-treated patients and 2.4% (2/83) of patients treated with a 4-oil mixed lipid emulsion. Most PNAC events occurred in patients who were treated for longer than 28 days.

The estimated cumulative incidence of PNAC is shown in the Kaplan-Meier cumulative incidence curve in Figure 1 [see Pediatric Clinical Studies (14.2)].

Figure 1: Cumulative Incidence Curve of Time to Parenteral Nutrition-Associated Cholestasis (PNAC) with Standard Error Bars

6.2 Postmarketing Experience

The following adverse reactions from voluntary reports have been reported with Intralipid. Because many of these reactions were reported voluntarily from a population of uncertain size, it is not always possible to reliably estimate their frequency or establish a causal relationship to drug exposure.

Cardiac disorders: palpitations
Gastrointestinal disorders: vomiting, nausea
General disorders and administration site conditions: chills, chest discomfort, pyrexia
Nervous system disorders: dizziness
Respiratory, thoracic, and mediastinal disorders: dyspnea
Immune system disorders: hypersensitivity reactions, including anaphylaxis [see Contraindications (4), Warnings and Precautions (5.3)]
Vascular disorders: phlebitis
Blood and lymphatic system disorders: hypercoagulability

7 DRUG INTERACTIONS

Soybean oil in Intralipid contains vitamin K1 which may counteract the anticoagulant activity of vitamin K antagonists such as warfarin. In patients who receive concomitant Intralipid and warfarin, increase monitoring of laboratory parameters for anticoagulant activity.

8 USE IN SPECIFIC POPULATIONS

8.1 Pregnancy

Risk Summary

Administration of the recommended dose of Intralipid is not expected to cause major birth defects, miscarriage, or other adverse maternal or fetal outcomes. No animal reproduction studies have been conducted with Intralipid. There are risks to the fetus associated with severe malnutrition during pregnancy (see Clinical Considerations).

The background risk of major birth defects and miscarriage for the indicated population(s) is unknown. All pregnancies have a background risk of birth defect, loss, or other adverse outcomes. In the U.S. general population, the estimated background risk of major birth defects and miscarriage in clinically recognized pregnancies is 2% to 4% and 15% to 20%, respectively.

Clinical Considerations

Disease-Associated Maternal and/or Embryo-Fetal Risk

Severe malnutrition in pregnant women is associated with preterm delivery, low birth weight, intrauterine growth restriction, congenital malformations, and perinatal mortality. Parenteral nutrition should be considered if the pregnant woman's nutritional requirements cannot be fulfilled by oral or enteral intake.

8.2 Lactation

Risk Summary

Administration of the recommended dose of Intralipid is not expected to cause harm to a breastfed infant. There are no data on the presence of Intralipid in human or animal milk or its effects on milk production. Available published literature includes fewer than five reported cases of breastfed infants exposed to various lipid emulsions via lactation, and these cases did not report adverse events. The developmental and health benefits of breastfeeding should be considered along with the mother's clinical need for Intralipid and any potential adverse effects of Intralipid on the breastfed infant, or from the underlying maternal condition.

8.4 Pediatric Use

Intralipid is contraindicated in pediatric patients with severe disorders of lipid metabolism [(see Contraindications (4)].

The safety and effectiveness of Intralipid have been established as a source of calories and essential fatty acids for PN in pediatric patients, including term and preterm neonates. Use of Intralipid in neonates is supported by evidence from short-term (i.e., 1- to 4- week) studies, and one study following neonates beyond 4 weeks [see Clinical Studies (14.2)]. Use of Intralipid in older pediatric patients is supported by evidence from short-term (i.e., <28 days) studies in pediatric patients 28 days to 12 years of age and additional evidence from studies in adults [see Clinical Studies (14)]. The most common adverse reactions in Intralipid-treated pediatric patients were anemia, vomiting, gamma-glutamyltransferase increased, and cholestasis. PNAC, a precursor to PNALD, developed more frequently in Intralipid-treated patients than in patients treated with a comparator 4-oil mixed lipid emulsion [see Warnings and Precautions (5.1) and Adverse Reactions (6.1)].

In the postmarketing setting, clinical decompensation with rapid infusion of intravenous lipid emulsion in neonates and infants, sometimes fatal, has been reported [see Warnings and Precautions (5.1)]. Because of immature renal function, preterm neonates receiving prolonged treatment with Intralipid may be at risk for aluminum toxicity [see Warnings and Precautions (5.8)].

8.5 Geriatric Use

Reported clinical experience has not identified differences in responses between the elderly and younger patients. In general, dose selection for an elderly patient should be cautious, usually starting at the low end of the dosing range, reflecting the greater frequency of decreased hepatic, renal, or cardiac function, and of concomitant disease or drug therapy.

10 OVERDOSAGE

In the event of an overdose, serious adverse reactions may result [see Warnings and Precautions (5.1, 5.5)]. Stop the infusion of Intralipid until triglyceride levels have normalized and symptoms have abated. The effects are usually reversible by stopping the lipid infusion. If medically appropriate, further intervention may be indicated. Lipids are not dialyzable from plasma.

11 DESCRIPTION

Intralipid is a sterile, non-pyrogenic, white, homogenous lipid emulsion for intravenous infusion as a source of calories and essential fatty acids. The lipid content of Intralipid is 0.2 g/mL and comprises soybean oil. The phosphate content is 15 mmol/L.

The total energy content, including fat, phospholipids, and glycerin is 2,000 kcal/L.

Each 100 mL of Intralipid contains approximately 20 g soybean oil, 1.2 g egg yolk phospholipids, 2.25 g glycerin, water for injection, and sodium hydroxide for pH adjustment (pH 6 to 8.9). Intralipid has an osmolality of approximately 350 mOsmol/kg water (which represents an osmolarity of 260 mOsmoL/L).

The soybean oil is a refined natural product consisting of a mixture of neutral triglycerides of predominantly unsaturated fatty acids with the following structure:

where are saturated and unsaturated fatty acid residues.

The major component fatty acids in Intralipid are linoleic acid (44% to 62%), oleic acid (19% to 30%), palmitic acid (7% to 14%), alpha-linolenic acid (4% to 11%), and stearic acid (1.4% to 5.5%). These fatty acids have the following chemical and structural formulas:

Purified egg phosphatides are a mixture of naturally occurring phospholipids which are isolated from the egg yolk. These phospholipids have the following general structure:

contain saturated and unsaturated fatty acids that abound in neutral fats. R3 is primarily either the choline or ethanolamine ester of phosphoric acid.

Glycerin is chemically designated C3H8O3 and is a clear colorless, hygroscopic syrupy liquid. It has the following structural formula:

The container-solution unit is a closed system and is not dependent upon entry of external air during administration. The container is overwrapped to provide protection from the physical environment and to provide an additional oxygen and moisture barrier when necessary.

Intralipid contains no more than 25 mcg/L of aluminum.

The container is not made with natural rubber latex, PVC, or DEHP.

12 CLINICAL PHARMACOLOGY

12.1 Mechanism of Action

Intralipid provides a biologically utilizable source of calories and essential fatty acids.

Fatty acids serve as an important substrate for energy production. The most common mechanism of action for energy production derived from fatty acid metabolism is beta oxidation. Fatty acids are also important for membrane structure and function, as precursors for bioactive molecules (such as prostaglandins), and as regulators of gene expression.

12.2 Pharmacodynamics

The pharmacodynamic effects of Intralipid have not been fully characterized.

12.3 Pharmacokinetics

Intralipid provides fatty acids in the form of triglycerides which are hydrolyzed by lipoprotein lipase to release free fatty acids. Linoleic acid and alpha-linolenic acid are metabolized within a common biochemical pathway through a series of desaturation and elongation steps.

13 NONCLINICAL TOXICOLOGY

13.1 Carcinogenesis, Mutagenesis, Impairment of Fertility

Carcinogenicity, genetic toxicology, and animal fertility studies have not been performed with Intralipid.

14 CLINICAL STUDIES

Intralipid or equivalent soybean oil lipid emulsion functioned as the comparator for the 4-oil mixed lipid emulsion in the clinical studies described in sections 14.1 and 14.2. The trial results are included to present the clinical experience with Intralipid.

14.1 Adult Clinical Studies

The efficacy of Intralipid or equivalent soybean oil lipid emulsion compared to a 4-oil mixed lipid emulsion was evaluated in 3 clinical studies in adult patients. Nutritional efficacy in adult studies was assessed by changes in anthropometric indices (body weight, height, and body mass index [BMI]), changes in lipid and protein metabolism (albumin), and fatty acid parameters. Of the 354 adult patients (178 Intralipid; 176 comparator), 62% were male, 99% were Caucasian, and ages ranged from 19 to 96 years. All patients received Intralipid/equivalent soybean oil lipid emulsion or the comparator as part of a PN regimen. Although Adult Study 1, Adult Study 2, and Adult Study 3 were not designed for formal statistical comparisons between Intralipid/equivalent soybean oil lipid emulsion and the comparator, they support Intralipid as a source of calories and essential fatty acids in adults. The lipid dosage was variable in these studies and adjusted to the patient's nutritional requirements.

Adult Study 1 was a double-blind, randomized, active-controlled, parallel-group, multicenter study in patients who required PN for at least 28 days. Seventy-five patients were enrolled, and 73 patients were treated with either Intralipid or the comparator. Changes in mean triglyceride levels from baseline values to Week 4 were similar in both the Intralipid and comparator groups. Mean albumin levels demonstrated a comparable decrease in both groups. Mean changes in body weight (kg) and BMI (kg/m2) were similar in both the Intralipid and the comparator groups.

Adult Study 2 was a phase 3, randomized, double-blind, active-controlled, multicenter study. A total of 249 postoperative adult patients were randomized to receive either an equivalent soybean oil lipid emulsion to Intralipid or the comparator for at least 5 days as part of their total parenteral nutrition (TPN) regimen. From baseline to Day 6, mean triglyceride levels increased similarly in both the soybean oil lipid emulsion and the comparator groups.

Adult Study 3 was a double-blind randomized, active-controlled, parallel-group, single-center study in 32 adult patients who required TPN for 10 to 14 days. Patients were treated with either an equivalent soybean oil lipid emulsion to Intralipid or the comparator. The increase in mean triglyceride levels from baseline to the final assessment was similar in both the soybean oil lipid emulsion and the comparator groups.

14.2 Pediatric Clinical Studies

The efficacy of Intralipid compared to a 4-oil mixed lipid emulsion in pediatric patients of all age groups, including term and preterm neonates, was evaluated in 333 patients in 4 randomized active-controlled, double-blind, parallel-group controlled clinical studies. Although Pediatric Studies 1, 2, 3, and 4 were not designed for formal statistical comparisons between Intralipid and the comparator, they support Intralipid as a source of calories and essential fatty acids in pediatric patients. The 333 pediatric patients (163 Intralipid; 170 comparator) consisted of 296 patients who were <28 days old, 22 patients 29 days to <2 years old, and 15 patients 2 to <12 years old. Fifty percent of the pediatric patients were male and 87% were Caucasian. All patients received Intralipid or the comparator as part of a PN regimen. Nutritional efficacy in neonates was assessed by changes in anthropometric indices (body weight, height, head circumference). Nutritional efficacy in pediatric patients, 28 days to 12 years of age, was assessed by changes in triglyceride concentrations and fatty acid parameters.

Pediatric Study 1 enrolled 152 preterm and term neonates (birth up to 28 days) and 9 patients ranging in age from 29 to 153 days. Patients were treated with either Intralipid (n=78) or the comparator (n=83). A total of 119 patients (58 Intralipid; 61 comparator) received study treatment for ≥14 days. A total of 27 patients received Intralipid for ≥29 days; 5 patients received Intralipid for the maximum study duration of 78-84 days.

Pediatric Studies 2 and 3 enrolled 60 and 84 preterm neonates, respectively, who were treated with either Intralipid or the comparator (72 neonates in each group). The median treatment duration for Intralipid group was 9 days in Pediatric Study 2 and 6 days in Pediatric Study 3.

Pediatric Study 4 enrolled 13 patients 5 months to <2 years of age and 15 patients 2 to 11.5 years of age. Patients were treated with either Intralipid (n=13) or the comparator (n=15) with a median treatment duration of 27 days.

In Pediatric Studies 1, 2 and 3, which enrolled neonates, Intralipid-treated patients showed increases in the median body weight, height/length, and head circumference (which was measured in Studies 1 and 3) comparable to the comparator-treated patients. Mean triglyceride levels from baseline to the final assessment in Pediatric Studies 1, 2, and 3 were variable in these neonates, but overall differences between groups were not considered clinically relevant. Mean triglyceride levels in Pediatric Study 4 were variable but remained within the normal range.

16 HOW SUPPLIED/STORAGE AND HANDLING

Intralipid 20% (lipid injectable emulsion, USP) is a sterile, homogeneous, milky, white lipid emulsion supplied in Flexible Containers as follows:

Product Code | Unit of Use | Unit of Sale
831800311 | NDC 65219-531-01 One 100 mL freeflex® bag | NDC 65219-531-10 Package of 10 freeflex® bags
831818311 | NDC 65219-533-01 One 250 mL freeflex® bag | NDC 65219-533-25 Package of 10 freeflex® bags
831826311 | NDC 65219-535-01 One 500 mL freeflex® bag | NDC 65219-535-50 Package of 12 freeflex® bags
831842311 | NDC 65219-539-01 One 1000 mL Pharmacy Bulk Package freeflex® bag | NDC 65219-539-10 Package of 6 freeflex® bags

Store below 25°C (77°F). Avoid excessive heat. Do not freeze. If accidentally frozen, discard container. Store in the overpouch until ready for use.

Intralipid 100 mL, 250 mL and 500 mL single-dose Flexible Containers

After removing the overpouch, infuse immediately. If not used immediately, the product should be stored at 2°C to 8°C (36°F to 46°F) for no longer than 24 hours. After removal from storage, infuse within 12 hours when using a Y-connector or within 24 hours if used as part of an admixture [see Dosage and Administration (2.2)].

Intralipid 1,000 mL Pharmacy Bulk Package

Use the Pharmacy Bulk Package immediately for admixing after removal from the overpouch. If not used immediately, the product should be stored for no longer than 24 hours at 2°C to 8°C (36°F to 46°F). After removal from storage, and once the closure is penetrated, use Pharmacy Bulk Package contents within 4 hours [see Dosage and Administration (2.2)].

Admixtures

Infuse admixtures containing Intralipid immediately. If not used immediately, admixtures should be stored at 2°C to 8°C (36°F to 46°F) for no longer than 24 hours. After removal from storage, infuse within 24 hours [see Dosage and Administration (2.2)].

Protect the admixed PN solution from light [see Dosage and Administration (2.2)].

17 PATIENT COUNSELING INFORMATION

When initiating Intralipid administration, discuss the following information with the patient or caregiver:

Clinical Decompensation with Rapid Infusion of Intravenous Lipid Emulsion in Neonates and Infants

Inform caregivers that acute respiratory distress and death may occur in neonates and infants after rapid infusion of intravenous lipid emulsions. If Intralipid is infused at home, instruct caregivers not to exceed the maximum infusion rate [see Warnings and Precautions (5.1)].

Parenteral Nutrition-Associated Liver Disease and Other Hepatobiliary Disorders

Inform patients and caregivers that use of parenteral nutrition may result in parenteral nutrition- associated liver disease and/or other hepatobiliary disorders [see Warnings and Precautions (5.2)].

Hypersensitivity Reactions

Inform patients and caregivers that Intralipid may cause hypersensitivity reactions, including anaphylaxis. If Intralipid is infused at home, instruct patients or caregivers to stop the infusion of Intralipid immediately and seek medical attention if they experience signs or symptoms of a hypersensitivity reaction, such as rapid or weak heartbeat, feeling faint, difficulty in breathing or swallowing, vomiting, nausea, headache, sweating, dizziness, hives, rash, itching, flushing, dizziness, fever, or chills [see Warnings and Precautions (5.3)].

Infections

Inform patients and caregivers that patients who receive Intralipid are at risk of infection. If Intralipid is infused at home, instruct patients or caregivers to ensure aseptic techniques are used for the preparation and administration of Intralipid and to monitor for signs and symptoms of infection [see Warnings and Precautions (5.4)].

Fat Overload Syndrome

Inform patients and caregivers that fat overload syndrome has been reported with the use of intravenous lipid emulsions. If Intralipid is infused at home, instruct patients or caregivers to stop the infusion of Intralipid if signs or symptoms of fat overload syndrome occur [see Warnings and Precautions (5.5)].

Refeeding Syndrome

If the patient is severely malnourished, inform patients and caregivers that administering parenteral nutrition including Intralipid may result in refeeding syndrome [see Warnings and Precautions (5.6)].

Hypertriglyceridemia

Inform patients and their caregivers about the risks of hypertriglyceridemia with Intralipid use [see Warnings and Precautions (5.7)].

Aluminum Toxicity

Inform patients and their caregivers that prolonged PN administration in patients with renal impairment, including preterm neonates, may result in aluminum reaching toxic levels associated with central nervous system and bone toxicity [see Warnings and Precautions (5.8)].

Preparation and Administration Instructions

If it is acceptable for a patient or caregiver to administer Intralipid at home, then provide recommendations on how to inspect and prepare, add compatible additives (when appropriate), administer, and store Intralipid [see Dosage and Administration (2.1, 2.2)]. Inform patients or caregivers not to deviate from the administration instructions given by the healthcare provider.

Manufactured by:

Uppsala, Sweden

Intralipid® is a registered trademark of Fresenius Kabi AB.
www.fresenius-kabi.com/us
451713C

PACKAGE LABEL

PACKAGE LABEL - PRINCIPAL DISPLAY - Intralipid 1000 mL Bag Label

NDC 65219-539-01

Intralipid® 20% 1000 ml

A 20% I.V. Fat Emulsion

1000 mL
Pharmacy Bulk Package

Not for Direct Infusion
For Intravenous Use
Rx only

PACKAGE LABEL – PRINCIPAL DISPLAY – Intralipid 1000 mL Shipper Label

NDC 65219-539-10

Intralipid® 20%

A 20% I.V. Fat Emulsion

Pharmacy Bulk Package

Not For Direct Infusion

1000 mL

For Intravenous Use

6 x 1000 mL